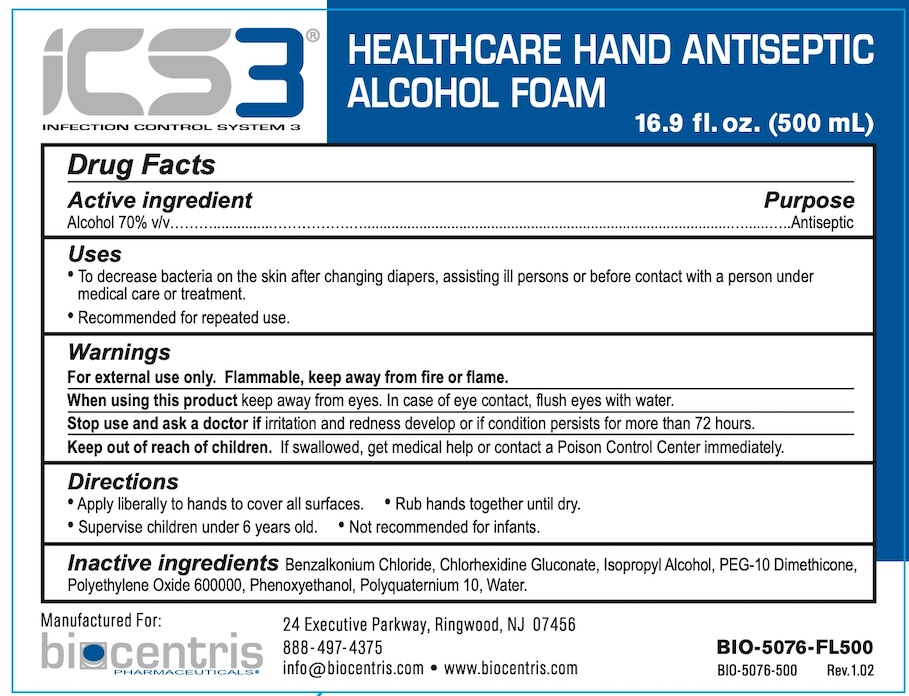 DRUG LABEL: ICS3 Blue Healthcare Hand Antiseptic
NDC: 81232-150 | Form: LIQUID
Manufacturer: Biocentris Pharmaceuticals, LLC
Category: otc | Type: HUMAN OTC DRUG LABEL
Date: 20220426

ACTIVE INGREDIENTS: ALCOHOL 70 mL/100 mL
INACTIVE INGREDIENTS: BENZALKONIUM CHLORIDE; CHLORHEXIDINE GLUCONATE; ISOPROPYL ALCOHOL; PEG-10 DIMETHICONE (600 CST); POLYETHYLENE OXIDE 600000; PHENOXYETHANOL; POLYQUATERNIUM-10 (30000 MPA.S AT 2%); WATER

Biocentris ICS3 Blue Healthcare Hand Antiseptic (70% Alcohol)

Drug Facts

Active ingredient

Alcohol 70% (v/v)

Purpose

Antiseptic

Uses

- To decrease bacteria on the skin after changing diapers, after assisting ill persons or before contact with a person under medical care or treatment.
- Recommended for repeated use.

Warnings

For external use only. Flammable. Keep away from fire or flame.

When using this product keep out of eyes. In case of eye contact, flush eyes with water.

Stop use and ask a doctor if irritation or redness develop or if condition persists for more than 72 hours.

Keep out of reach of children. If swallowed, get medical help or contact a Poison Control Center immediately.

Directions

- Apply liberally to hands to cover all surfaces.
- Rub hands together until dry.
- Supervise children under 6 years old.
- Not recommended for infants.

INACTIVE INGREDIENT

Inactive ingredients Benzalkonium Chloride, Chlorhexidine Gluconate, Isopropyl Alcohol, PEG-10 Dimethicone, Polyethylene Oxide 600000, Phenoxyethanol, Polyquaternium 10, Water

Manufactured for:

biocentris PHARMACEUTICALS

24 Executive Parkway, Ringwood, NJ 07456

888-497-4375

info@biocentris.com • www.biocentris.com

PACKAGE LABEL

ICS3®

INFECTION CONTROL SYSTEM 3

HEALTHCARE HAND ANTISEPTIC

ALCOHOL FOAM

16.9 fl. oz. (500 mL)